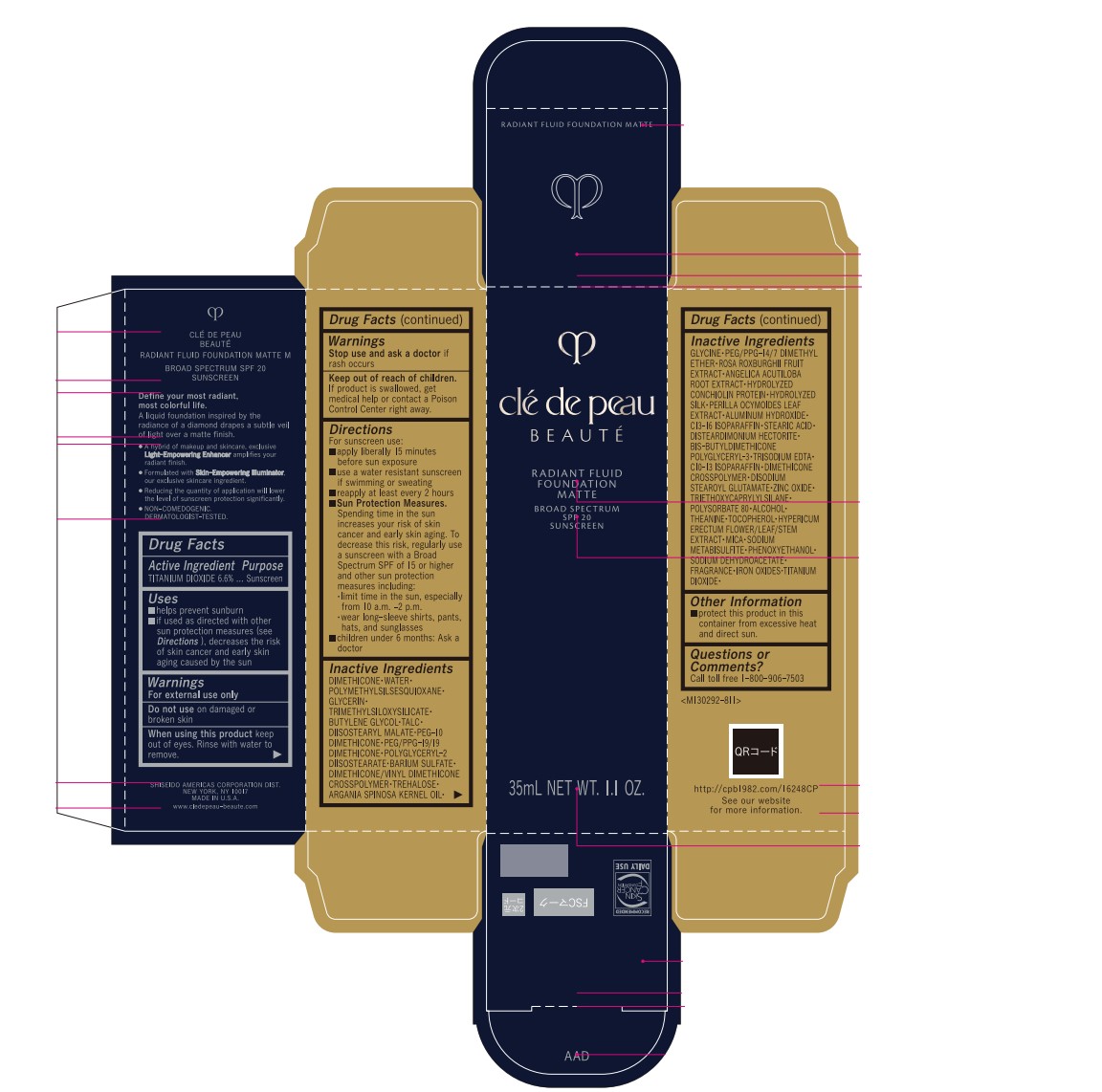 DRUG LABEL: CLE DE PEAU BEAUTE RADIANT FLUID FOUNDATION MATTE M
NDC: 58411-926 | Form: CREAM
Manufacturer: Shiseido Americas Corporation
Category: otc | Type: HUMAN OTC DRUG LABEL
Date: 20260226

ACTIVE INGREDIENTS: TITANIUM DIOXIDE 2.73735 g/35 mL
INACTIVE INGREDIENTS: DIMETHICONE; WATER; POLYMETHYLSILSESQUIOXANE (11 MICRONS); GLYCERIN; TRIMETHYLSILOXYSILICATE (M/Q 0.6-0.8); BUTYLENE GLYCOL; TALC; DIISOSTEARYL MALATE; PEG-10 DIMETHICONE (200 CST); PEG/PPG-19/19 DIMETHICONE; POLYGLYCERYL-2 DIISOSTEARATE; BARIUM SULFATE; DIMETHICONE/VINYL DIMETHICONE CROSSPOLYMER (HARD PARTICLE); TREHALOSE; ARGANIA SPINOSA KERNEL OIL; GLYCINE; PEG/PPG-14/7 DIMETHYL ETHER; ROSA ROXBURGHII FRUIT; ANGELICA ACUTILOBA ROOT; PERILLA FRUTESCENS LEAF; ALUMINUM HYDROXIDE; C13-16 ISOPARAFFIN; STEARIC ACID; DISTEARDIMONIUM HECTORITE; TRISODIUM EDTA; DIMETHICONE CROSSPOLYMER; DISODIUM STEAROYL GLUTAMATE; ZINC OXIDE; TRIETHOXYCAPRYLYLSILANE; POLYSORBATE 80; ALCOHOL; THEANINE; TOCOPHEROL; HYPERICUM ERECTUM WHOLE; MICA; SODIUM METABISULFITE; PHENOXYETHANOL; SODIUM DEHYDROACETATE; FERRIC OXIDE RED

CLE DE PEAU BEAUTE RADIANT FLUID FOUNDATION MATTE M

Drug Facts

Active ingredients | Purpose
TITANIUM DIOXIDE 6.6% | Sunscreen

INDICATIONS AND USAGE

- helps prevent sunburn
- if used as directed with other sun protection measures (see Directions), decreases the risk of skin cancer and early skin aging caused by the sun

Warnings

For external use only

Do not use on damaged or broken skin

When using this product keep out of eyes. Rinse with water to remove

Stop use and ask a doctor if rash occurs

Keep out of reach of children. If product is swallowed, get medical help or contact a Poison Control Center right away.

Directions

For sunscreen use:

- apply liberally 15 minutes before sun exposure
- use a water resistant sunscreen if swimming or sweating
- reapply at least every 2 hours
- Sun Protection Measure. Spending time in the sun increases your risk of skin cancer and early skin aging. To decrease this risk, regularly use a sunscreen with a Broad Spectrum SPF of 15 or higher and other sun protection measures including:
- limit time in the sun, especially from 10 a.m. - 2 p.m.
- wear long-sleeve shirts, pants, hats, and sunglasses
- children under 6 months: Ask a doctor

INACTIVE INGREDIENT

DIMETHICONE • WATER • POLYMETHYLSILSESQUIOXANE • GLYCERIN • TRIMETHYLSILOXYSILICATE • BUTYLENE GLYCOL • TALC • DIISOSTEARYL MALATE • PEG-10 DIMETHICONE • PEG/PPG-19/19 DIMETHICONE • POLYGLYCERYL-2 DIISOSTEARATE • BARIUM SULFATE • DIMETHICONE/VINYL DIMETHICONE CROSSPOLYMER • TREHALOSE • ARGANIA SPINOSA KERNEL OIL • GLYCINE • PEG/PPG-14/7 DIMETHYL ETHER • ROSE ROXBURGHII FRUIT EXTRACT • ANGELICA ACUTILOBA ROOT EXTRACT • HYDROLYZED CONCHIOLIN PROTEIN • HYDROLYZED SILK • PERILLA OCYMOIDES LEAF EXTRACT • AMMONIUM HYDROXIDE • C13-16 ISOPARAFFIN • STEARIC ACID • DISTEARDIMONIUM HECTORITE • BIS-BUTYLDIMETHICONE POLYGLYCERYL-3 • TRISODIUM EDTA • C10-13 ISOPARAFFIN • DIMETHICONE CROSSPOLYMER • DISODIUM STEAROYL GLUTAMATE • ZINC OXIDE • TRIETHOXYCAPRYLYLSILANE • POLYSORBATE 80 • ALCOHOL • THEANINE • TOCOPHEROL• HYPERICUM ERECTUM FLOWER/LEAF/STEM EXTRACT • MICA • SODIUM METABISULFITE • PHENOXYETHANOL • SODIUM DEHYDROACETATE • FRAGRANCE • IRON OXIDES • TITANIUM DIOXIDE •

Other information

- protect this product in this container from excessibe heat and direct sunlight

Questions or Comments?

Call toll free 1-800-906-7503

PRINCIPAL DISPLAY PANEL - 35 mL Vial Carton - B10

clé de peau

BEAUTÉ

Radiant Fluid

Foundation

Matte

Broad Spectrum

SPF 20

Sunscreen

PRINCIPAL DISPLAY PANEL - 35 mL Vial Carton - B100

clé de peau

BEAUTÉ

Radiant Fluid

Foundation

Matte

Broad Spectrum

SPF 20

Sunscreen

PRINCIPAL DISPLAY PANEL - 35 mL Vial Carton - B20

clé de peau

BEAUTÉ

Radiant Fluid

Foundation

Matte

Broad Spectrum

SPF 20

Sunscreen

PRINCIPAL DISPLAY PANEL - 35 mL Vial Carton - B30

clé de peau

BEAUTÉ

Radiant Fluid

Foundation

Matte

Broad Spectrum

SPF 20

Sunscreen

PRINCIPAL DISPLAY PANEL - 35 mL Vial Carton - B40

clé de peau

BEAUTÉ

Radiant Fluid

Foundation

Matte

Broad Spectrum

SPF 20

Sunscreen

PRINCIPAL DISPLAY PANEL - 35 mL Vial Carton - B50

clé de peau

BEAUTÉ

Radiant Fluid

Foundation

Matte

Broad Spectrum

SPF 20

Sunscreen

PRINCIPAL DISPLAY PANEL - 35 mL Vial Carton - B60

clé de peau

BEAUTÉ

Radiant Fluid

Foundation

Matte

Broad Spectrum

SPF 20

Sunscreen

PRINCIPAL DISPLAY PANEL - 35 mL Vial Carton - B70

clé de peau

BEAUTÉ

Radiant Fluid

Foundation

Matte

Broad Spectrum

SPF 20

Sunscreen

PRINCIPAL DISPLAY PANEL - 35 mL Vial Carton - B80

clé de peau

BEAUTÉ

Radiant Fluid

Foundation

Matte

Broad Spectrum

SPF 20

Sunscreen

PRINCIPAL DISPLAY PANEL - 35 mL Vial Carton - B90

clé de peau

BEAUTÉ

Radiant Fluid

Foundation

Matte

Broad Spectrum

SPF 20

Sunscreen

PRINCIPAL DISPLAY PANEL - 35 mL Vial Carton - BF10

clé de peau

BEAUTÉ

Radiant Fluid

Foundation

Matte

Broad Spectrum

SPF 20

Sunscreen

PRINCIPAL DISPLAY PANEL - 35 mL Vial Carton - BF50

clé de peau

BEAUTÉ

Radiant Fluid

Foundation

Matte

Broad Spectrum

SPF 20

Sunscreen

PRINCIPAL DISPLAY PANEL - 35 mL Vial Carton - BF60

clé de peau

BEAUTÉ

Radiant Fluid

Foundation

Matte

Broad Spectrum

SPF 20

Sunscreen

PRINCIPAL DISPLAY PANEL - 35 mL Vial Carton - I10

clé de peau

BEAUTÉ

Radiant Fluid

Foundation

Matte

Broad Spectrum

SPF 20

Sunscreen

PRINCIPAL DISPLAY PANEL - 35 mL Vial Carton - O10

clé de peau

BEAUTÉ

Radiant Fluid

Foundation

Matte

Broad Spectrum

SPF 20

Sunscreen

PRINCIPAL DISPLAY PANEL - 35 mL Vial Carton - O100

clé de peau

BEAUTÉ

Radiant Fluid

Foundation

Matte

Broad Spectrum

SPF 20

Sunscreen

PRINCIPAL DISPLAY PANEL - 35 mL Vial Carton - O20

clé de peau

BEAUTÉ

Radiant Fluid

Foundation

Matte

Broad Spectrum

SPF 20

Sunscreen

PRINCIPAL DISPLAY PANEL - 35 mL Vial Carton - O30

clé de peau

BEAUTÉ

Radiant Fluid

Foundation

Matte

Broad Spectrum

SPF 20

Sunscreen

PRINCIPAL DISPLAY PANEL - 35 mL Vial Carton - O40

clé de peau

BEAUTÉ

Radiant Fluid

Foundation

Matte

Broad Spectrum

SPF 20

Sunscreen

PRINCIPAL DISPLAY PANEL - 35 mL Vial Carton - O50

clé de peau

BEAUTÉ

Radiant Fluid

Foundation

Matte

Broad Spectrum

SPF 20

Sunscreen

PRINCIPAL DISPLAY PANEL - 35 mL Vial Carton - O60

clé de peau

BEAUTÉ

Radiant Fluid

Foundation

Matte

Broad Spectrum

SPF 20

Sunscreen

PRINCIPAL DISPLAY PANEL - 35 mL Vial Carton - O70

clé de peau

BEAUTÉ

Radiant Fluid

Foundation

Matte

Broad Spectrum

SPF 20

Sunscreen

PRINCIPAL DISPLAY PANEL - 35 mL Vial Carton - O80

clé de peau

BEAUTÉ

Radiant Fluid

Foundation

Matte

Broad Spectrum

SPF 20

Sunscreen

PRINCIPAL DISPLAY PANEL - 35 mL Vial Carton - O90

clé de peau

BEAUTÉ

Radiant Fluid

Foundation

Matte

Broad Spectrum

SPF 20

Sunscreen